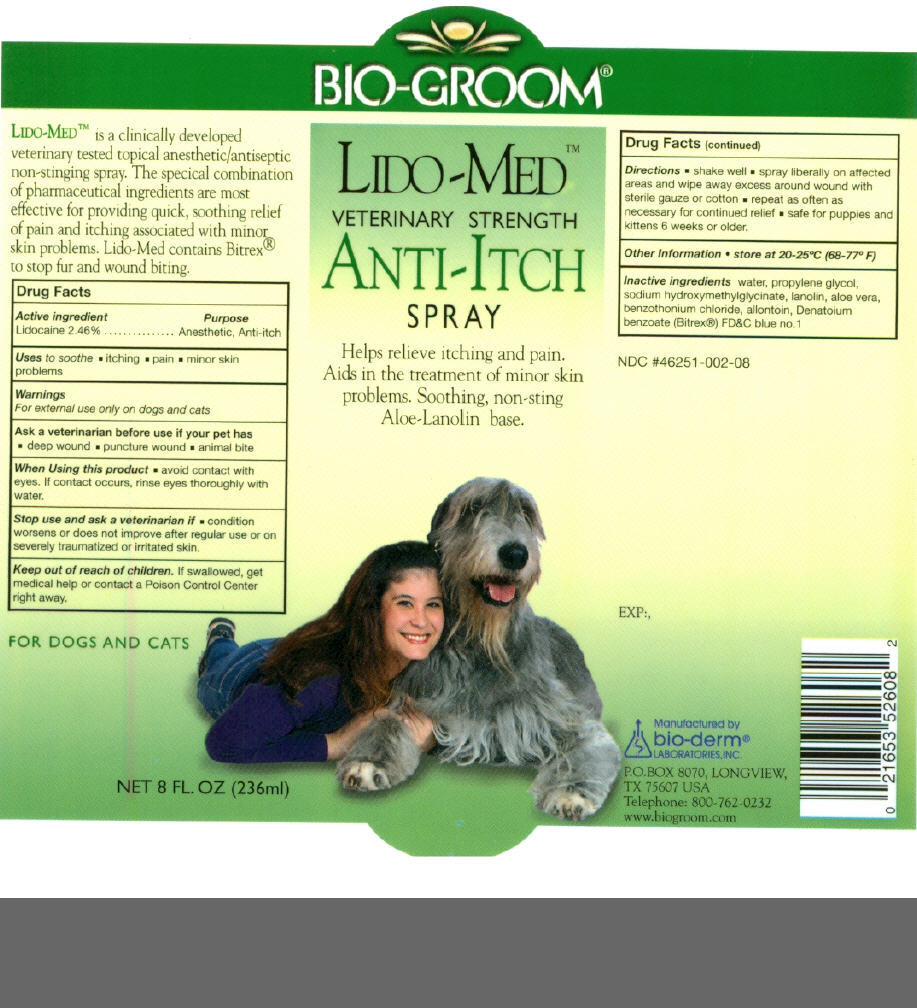 DRUG LABEL: Bio-Groom Lido-Med 
NDC: 46521-002 | Form: SPRAY
Manufacturer: Bio-Derm Laboratories Inc.
Category: animal | Type: OTC ANIMAL DRUG LABEL
Date: 20110610

ACTIVE INGREDIENTS: LIDOCAINE 2.46 mg/100 mL
INACTIVE INGREDIENTS: WATER; PROPYLENE GLYCOL; SODIUM HYDROXYMETHYLGLYCINATE; LANOLIN; ALOE; BENZETHONIUM CHLORIDE; ALLANTOIN; DENATONIUM BENZOATE; FD&C BLUE NO. 1

Bio-Groom
Lido-Med Anti-Itch Spray
Net 4 Fl Oz (118 ml)

Drug Facts

Active Ingredient

Lidocaine 2.46%

Purpose

Anesthetic, Anti-itch

Uses

to soothe

- itching
- pain
- minor skin problems

Warnings

For external use only on dogs and cats

Ask a veterinarian before use if your pet has

- deep wound
- puncture wound
- animal bite

When using this product

- avoid contact with eyes. If contact occurs rinse eyes thoroughly with water.

Stop use and ask a veterinarian if

- condition worsens or does not improve after regular use or on severely traumatized or irritated skin.

Keep out of reach of children. If swallowed, get medical help or contact a Poison Control Center right away.

Directions

- shake well
- spray liberally on affected areas and wipe away excess around wound with sterile gauze or cotton
- repeat as often as necessary for continued relief
- safe for puppies and kittens 6 weeks or older

Other Information

- store at 20-25°C (68-77°F)

Inactive ingredients

water, propylene glycol, sodium hydroxymethylglycinate, lanolin, aloe vera, benzethonium chloride, allantoin, Denatoium benzoate (Bitrex®) FD&C blue no. 1

Manufactured by
bio-derm®
LABORATORIES, INC.

P.O.BOX 8070, LONGVIEW,
TX 75607 USA

PRINCIPAL DISPLAY PANEL - 118 ml Bottle Label

BIO-GROOM®

LIDO-MED™
VETERINARY STRENGTH

ANTI-ITCH
SPRAY

Helps relieve itching and pain.
Aids in the treatment of minor skin
problems. Soothing, non-sting
Aloe-Lanolin base.